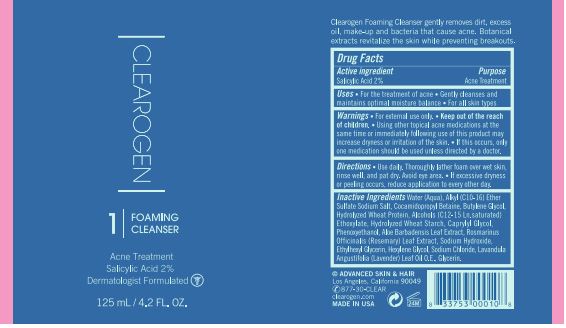 DRUG LABEL: Foaming Cleanser
NDC: 62742-4239 | Form: LIQUID
Manufacturer: Allure Labs
Category: otc | Type: HUMAN OTC DRUG LABEL
Date: 20231207

ACTIVE INGREDIENTS: SALICYLIC ACID 2 g/100 g
INACTIVE INGREDIENTS: C12-15 ALCOHOLS; CAPRYLYL GLYCOL; SODIUM HYDROXIDE; 1-ETHOXYUNDECANE; WATER; COCAMIDOPROPYL BETAINE; BUTYLENE GLYCOL; HYDROLYZED WHEAT PROTEIN (ENZYMATIC, 3000 MW); ALOE VERA LEAF; ROSEMARY; (C10-C16)ALKYLDIMETHYLAMINE OXIDE; STARCH, WHEAT; ETHYLHEXYLGLYCERIN; SODIUM CHLORIDE; PHENOXYETHANOL; HEXYLENE GLYCOL; LAVANDULA ANGUSTIFOLIA SUBSP. ANGUSTIFOLIA LEAF; GLYCERIN

Drug Facts

Active Ingredient:

Salicylic Acid 2%

Purpose: Acne Treatment

INDICATIONS AND USAGE

Uses: For the treatment of acne

Gently cleanses and maintains optimal moisture balance.

For all skin types

WARNINGS

Warning: For external use only

DO NOT USE

If excessive dryness or peeling occurs

WHEN USING

Avoid eye area

STOP USE

If excessive dryness or peeling occurs

Keep out of reach of children.

DOSAGE AND ADMINISTRATION

Direction:

Use daily. Thoroughly lather foam over wet skin, rinse well and pat dry. Avoid eye area. If excessive dryness or peeling occurs, reduce application to every other day.

OTHER SAFETY INFORMATION

Using other topical acne medication at the same time or immediately following use of this product may increase dryness or irritation of the skin.

If this occurs, only one medication should be used unless directed by a doctor.

Inactive Ingredient:

Water (Aqua), Alkyl (C10-16) Ether Sulfate Sodium Salt, Cocamidopropyl Betaine, Butylene Glycol, Hydrolyzed Wheat Protein, Alcohol (C12-15 Ln. saturated), Ethoxylate, Hydrolyzed Wheat Starch, Caprylyl Glycol, Phenoxyethanol, Aloe Barbadensis Leaf Extract, Rosmarinus Officinalis (Rosemary) Leaf Extract, Sodium Hydroxide, Ethylhexyl Glycerin, Hexylene Glycol, Sodium Chloride, Lavandula Angustifolia (Lavender) Leaf Oil O.E., Glycerin.